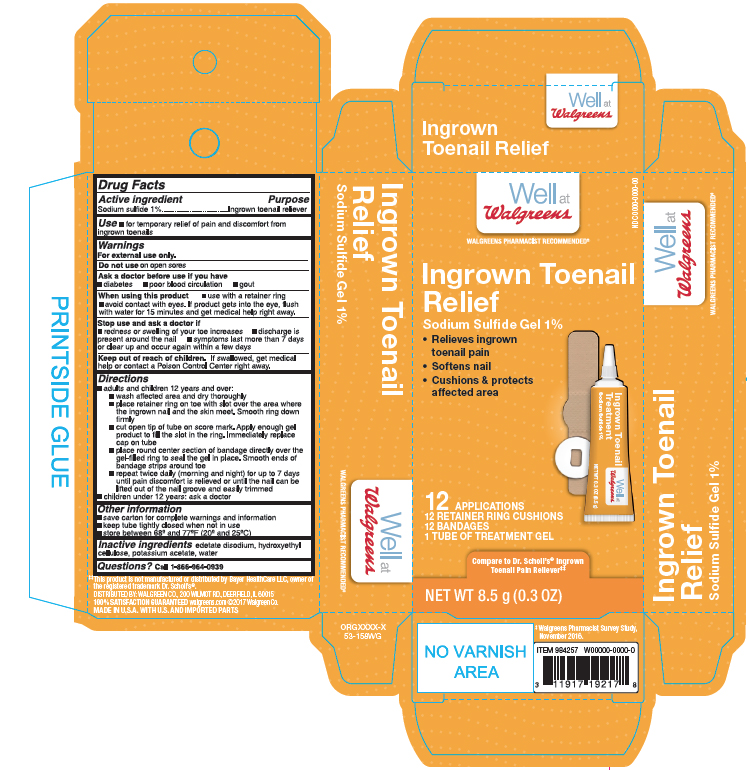 DRUG LABEL: Sodium Sufide
NDC: 0363-9560 | Form: GEL
Manufacturer: Walgreens Company
Category: otc | Type: HUMAN OTC DRUG LABEL
Date: 20170317

ACTIVE INGREDIENTS: SODIUM SULFIDE 0.085 g/8.5 g
INACTIVE INGREDIENTS: EDETATE DISODIUM; POTASSIUM ACETATE; WATER

Ingrown Toenail Relief

Active ingredient

Sodium Sufide 1%

Purpose

Ingrown Toenail Pain Reliever

Use

- for the temporary releif of pain and discomfort from ingrown toenails

WARNINGS

For external use only.

Do not use

on open sores.

Ask a doctor before use if you have

- diabetes
- poor blood circulation
- gout

When using this product

- use with a retainer ring
- avoid contact with eyes. If prodcut gets into the eye, flush with water for 15 minutes and get medical help reight away.

Stop use and ask a doctor if

- redness or swelling of your toe increases
- discharge is present around the nail
- symptoms last more than 7 days or clear up and occur again within a few days

Keep out of reach of children

If swallowed, get medical help or contact a Poison Control Center right away.

Directions

adults and children 12 yers and over:

- wash affected area and dry thoroghly
- place retainer ring on toe with slot over the area where the ingrown nail and the skin meet. Smooth ring down firmly
- cut open tip of the tube on score mark. Apply enough gel prodcut to fill the slot in the ring. Immeciately replace cap on tube
- place round center section of bandage directly over the gel- filled ring to seal the gel in place. Smooth ends of bandage strips around toe
- repeat twice daily (morning and night) for up to 7 days until pain discomfort is relieved or until the nail can be lifted out of the nail groove and easliy trimmed

Children under 12 years: ask a doctor

Other Information

- save carton for complete warnings and information
- keep tube tightly closed when not in use
- store between 68o anf 77oF (20o and 25oC)

Inactive Ingredient

edetate disodium, hydroxyethyl cellulose, pottasium acetate, water

Questions?

Call 1-866-964-0939

Principal Display Panel

Well at Walgreens

Ingrown Toenail Relief

Sodium Sulfide Gel 1%

- Relieves ingrown toenail pain
- Softens nail
- Cushions & protects afftected area

12APPLICATIONS

12 RETAINER RING CUSHIONS

12 BANDAGES

1 TUBE OF TREATMENT GEL

NET WT 8.5 g(0.3 OZ)